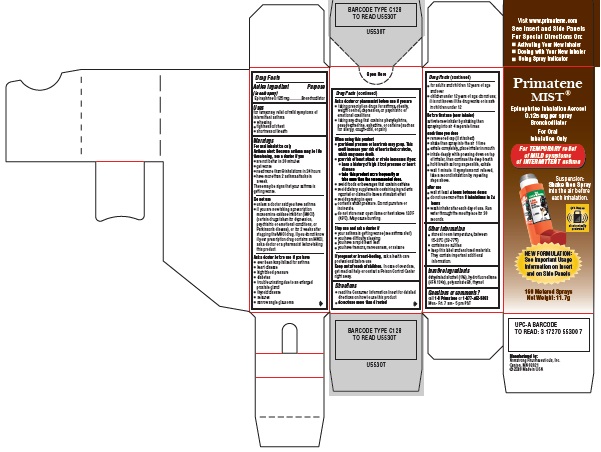 DRUG LABEL: Primatene Mist
NDC: 17270-5530 | Form: AEROSOL
Manufacturer: Armstrong Pharmaceuticals, Inc.
Category: otc | Type: HUMAN OTC DRUG LABEL
Date: 20200701

ACTIVE INGREDIENTS: EPINEPHRINE 125 ug/1 1
INACTIVE INGREDIENTS: ALCOHOL; NORFLURANE; POLYSORBATE 80; THYMOL

Active ingredient (in each spray)

Epinephrine 0.125 mg

Purpose

Bronchodilator

Uses

for temporary relief of mild symptoms of intermittent asthma
■ wheezing
■ tightness of chest
■ shortness of breath

Warnings

For oral inhalation only
Asthma alert: Because asthma may be life threatening, see a doctor if you
■ are not better in 20 minutes
■ get worse
■ need more than 8 inhalations in 24 hours
■ have more than 2 asthma attacks in a week
These may be signs that your asthma is
getting worse.

Do not use

■ unless a doctor said you have asthma
■ if you are now taking a prescription monoamine oxidase inhibitor (MAOI) (certain drugs taken for depression, psychiatric or emotional conditions, or Parkinson’s disease), or for 2 weeks after stopping the MAOI drug. If you do not know if your prescription drug contains an MAOI, ask a doctor or a pharmacist before taking this product.

Ask a doctor before use if you have

■ ever been hospitalized for asthma
■ heart disease
■ high blood pressure
■ diabetes
■ trouble urinating due to an enlarged prostate gland
■ thyroid disease
■ seizures
■ narrow angle glaucoma

Ask a doctor or pharmacist before use if you are

■ taking prescription drugs for asthma, obesity, weight control, depression, or psychiatric or emotional conditions
■ taking any drug that contains phenylephrine, pseudoephedrine, ephedrine, or caffeine (such as for allergy, cough-cold, or pain)

When using this product

■ your blood pressure or heart rate may go up. This could increase your risk of heart attack or stroke, which may cause death.
■ your risk of heart attack or stroke increases if you:
■ have a history of high blood pressure or heart disease
■ take this product more frequently or take more than the recommended dose.
■ avoid foods or beverages that contain caffeine
■ avoid dietary supplements containing ingredients reported or claimed to have a stimulant effect
■ avoid spraying in eyes
■ contents under pressure. Do not puncture or incinerate.
■ do not store near open flame or heat above 120°F (49°C). May cause bursting.

Stop use and ask a doctor if

■ your asthma is getting worse (see asthma alert)
■ you have difficulty sleeping
■ you have a rapid heart beat
■ you have tremors, nervousness, or seizure

PREGNANCY OR BREAST FEEDING

If pregnant or breast-feeding, ask a health care professional before use

Keep out of reach of children. In case of overdose, get medical help or contact a Poison Control Center right away.

Directions

■ read the Consumer Information Insert for detailed directions on how to use this product
■ do not use more than directed

■ for adults and children 12 years of age and over
■ children under 12 years of age: do not use; it is not known if the drug works or is safe in children under 12

Before first use (new inhaler)
activate new inhaler by shaking then spraying into air 4 separate times

each time you dose
■ remove red cap (if attached)
■ shake then spray into the air 1 time
■ exhale completely, place inhaler in mouth
■ inhale deeply while pressing down on top of inhaler, then continue the deep breath
■ hold breath as long as possible, exhale
■ wait 1 minute. If symptoms not relieved, take a second inhalation by repeating steps above.

after use
■ wait at least 4 hours between doses
■ do not use more than 8 inhalations in 24 hours
■ wash inhaler after each day of use. Run water through the mouthpiece for 30 seconds.

Other information

■ store at room temperature, between 15-25°C (59-77°F)
■ contains no sulfites
■ keep this label and enclosed materials. They contain important additional information.

Inactive ingredients

dehydrated alcohol (1%), hydrofluoroalkane (HFA 134a), polysorbate 80, thymol

Questions or comments?

call 1-8 Primatene or 1-877-462-8363

Mon.- Fri. 7 am - 5 pm PST

Primatene MIST® Carton

Principal Display Panel Text:

Primatene MIST®

Epinephrine Inhalation Aerosol
0.125 mg per spray
Bronchodilator
For Oral
Inhalation Only

For TEMPORARY relief
of MILD symptoms
of INTERMITTENT asthma

Suspension:
Shake then Spray
into the air before
each inhalation.

This item is

electronically

protected

NEW FORMULATION:
See Important Usage
Information on Insert
and on Side Panels

160 Metered Sprays
Net Weight: 11.7g